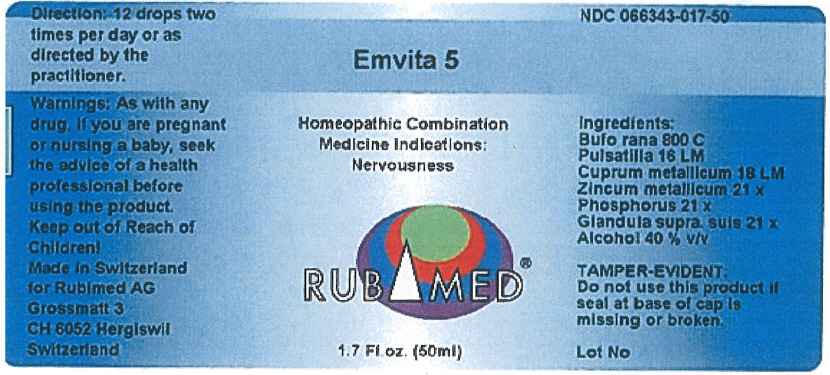 DRUG LABEL: Emvita 5
NDC: 66343-017 | Form: LIQUID
Manufacturer: RUBIMED AG
Category: otc | Type: HUMAN OTC DRUG LABEL
Date: 20150709

ACTIVE INGREDIENTS: Bufo Bufo Cutaneous Gland 800 [hp_C]/1 mL; Pulsatilla Vulgaris 16 [hp_M]/1 mL; Copper 18 [hp_M]/1 mL; Zinc 21 [hp_X]/1 mL; Phosphorus 21 [hp_X]/1 mL; Sus Scrofa Adrenal Gland 21 [hp_X]/1 mL
INACTIVE INGREDIENTS: Alcohol 0.4 mL/1 mL

Emvita 5

PURPOSE

Homeopathic Combination Medicine Indications: Nervousness

Ingredients

INACTIVE INGREDIENT

Bufo rang 800 C
Pulsatilla 16 LM
Cuprum metallicum 18 LM
Zincum metallicum 21 x
Phosphorus 21 x
Glandula supra suis 21 x
Alcohol 40 % v/v

TAMPER-EVIDENT

Do not use this product if seal at base of cap is missing or broken.

Direction

12 drops two times per day or as directed by the practitioner.

Warnings

PREGNANCY OR BREAST FEEDING

As with any drug, if you are pregnant or nursing a baby, seek the advice of a health professional before using the product.

Keep out of Reach of Children!

PRINCIPAL DISPLAY PANEL - 50 ml Bottle Label

Emvita 5

Homeopathic Combination
Medicine Indications:
Nervousness

RUBIMED®

1.7 Fl.oz. (50ml)